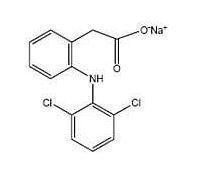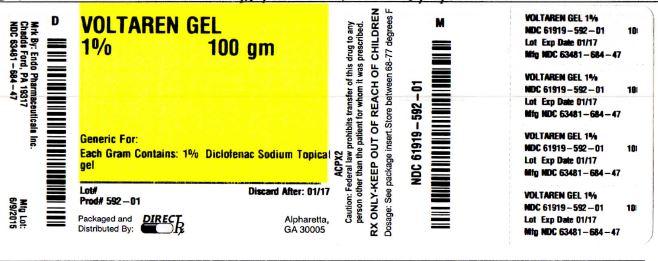 DRUG LABEL: VOLTAREN
NDC: 61919-592 | Form: GEL
Manufacturer: DIRECT RX
Category: prescription | Type: HUMAN PRESCRIPTION DRUG LABEL
Date: 20150810

ACTIVE INGREDIENTS: DICLOFENAC SODIUM 10 mg/1 g
INACTIVE INGREDIENTS: AMMONIA; CARBOMER HOMOPOLYMER TYPE C; ISOPROPYL ALCOHOL; MINERAL OIL; POLYOXYL 20 CETOSTEARYL ETHER; PROPYLENE GLYCOL; WATER

VOLTAREN

BOXED WARNING SECTION

WARNING: CARDIOVASCULAR AND GASTROINTESTINAL RISK

Cardiovascular Risk

- Nonsteroidal anti-inflammatory drugs (NSAIDs) may cause an increased risk of serious cardiovascular thrombotic events, myocardial infarction, and stroke, which can be fatal. This risk may increase with duration of use. Patients with cardiovascular disease or risk factors for cardiovascular disease may be at greater risk [see Warnings and Precautions (5.1)].
- Voltaren® Gel is contraindicated for the treatment of peri-operative pain in the setting of coronary artery bypass graft (CABG) surgery [see Contraindications (4)].

Gastrointestinal Risk

- NSAIDs cause an increased risk of serious gastrointestinal adverse events including bleeding, ulceration, and perforation of the stomach or intestines, which can be fatal. These events can occur at any time during use and without warning symptoms. Elderly patients are at greater risk for serious gastrointestinal events [see Warnings and Precautions(5.2)].

INDICATIONS & USAGE SECTION

Voltaren® Gel is indicated for the relief of the pain of osteoarthritis of joints amenable to topical treatment, such as the knees and those of the hands.

- Voltaren® Gel has not been evaluated for use on the spine, hip, or shoulder.

DOSAGE & ADMINISTRATION SECTION

2.1 Dosing Card [See the Medication Guide – Patient Instructions for Use]

The proper amount of Voltaren® Gel should be measured using the dosing card supplied in the drug product carton. The dosing card is made of polypropylene, like the tube cap containing Voltaren® Gel, but without the white colorant. The dosing card should be used for each application of drug product. The gel should be applied within the oblong area of the dosing card up to the 2 gram or 4 gram line (2 g for each elbow, wrist, or hand, and 4 g for each knee, ankle, or foot). The dosing card containing Voltaren® Gel can be used to apply the gel. The hands should then be used to gently rub the gel into the skin. After using the dosing card, hold with fingertips, rinse, and dry. It treatment site is the hands, patients should wait at least one (1) hour to wash their hands

2.2 Lower extremities, including the knees, ankles, and feet

Apply the gel (4 g) to the affected foot or knee or ankle, 4 times daily. Voltaren® Gel should be gently massaged into the skin ensuring application to the entire affected foot or knee or ankle. The entire foot includes the sole, top of the foot and the toes. Do not apply more than 16 g daily to any single joint of the lower extremities.

2.3 Upper extremities including the elbows, wrists and hands

Apply the gel (2 g) to the affected hand or elbow or wrist, 4 times daily. Voltaren® Gel should be gently massaged into the skin ensuring application to the entire affected hand or elbow or wrist. The entire hand includes the palm, back of the hands, and the fingers. Do not apply more than 8 g daily to any single joint of the upper extremities.

Total dose should not exceed 32 g per day, over all affected joints.

2.4 Special Precautions

- Showering/bathing should be avoided for at least 1 hour after the application. Patient should wash his/her hands after use, unless the hands are the treated joint. If Voltaren® Gel is applied to the hand(s) for treatment; patient should not wash the treated hand(s) for at least 1 hour after the application.
- Voltaren® Gel should not be applied to open wounds.
- Contact of Voltaren® Gel with eyes and mucous membranes should be avoided.
- External heat and/or occlusive dressings should not be applied to treated joints.
- Exposure of the treated joint(s) to sunlight should be avoided.
- Voltaren® Gel should not be used concomitantly with sunscreens, cosmetics, lotions, moisturizers, insect repellants, or other topical medications on the same skin sites has not been evaluated.
- Concomitant use of Voltaren® Gel with oral non-steroidal anti-inflammatory drugs (NSAIDs) has not been evaluated, and may increase adverse NSAIDs effects.
- Wearing of clothing or gloves should be avoided for at least 10 minutes after applying Voltaren® Gel.

CONTRAINDICATIONS SECTION

The use of Voltaren® Gel is contraindicated in patients with a known hypersensitivity to diclofenac.

Voltaren® Gel should not be administered in patients who have experienced asthma, urticaria, or other allergic-type reactions after taking aspirin or other NSAIDs. Severe, rarely fatal, anaphylactic-like reactions to NSAIDs have been reported in such patients [see Warnings and Precautions (5.1)].

Voltaren® Gel is contraindicated in the setting of coronary artery bypass graft (CABG) surgery [see Warnings and Precautions (5.1)].

WARNINGS AND PRECAUTIONS SECTION

5.1 Cardiovascular Thrombotic Events

Clinical trials of several COX-2 selective and nonselective NSAIDs of up to three years duration have shown an increased risk of serious cardiovascular (CV) thrombotic events, myocardial infarction, and stroke, which can be fatal. All NSAIDs, both COX-2 selective and nonselective, may have a similar risk. Patients with known CV disease or risk factors for CV disease may be at greater risk. To minimize the potential risk for an adverse CV event in patients treated with NSAIDs, the lowest effective dose should be used for the shortest duration possible. Physicians and patients should remain alert for the development of such events, even in the absence of previous CV symptoms. Patients should be informed about the signs and/or symptoms of serious CV toxicity and the steps to take if they occur.

There is no consistent evidence that concurrent use of aspirin mitigates the increased risk of serious CV thrombotic events associated with NSAIDs use. The concurrent use of aspirin and NSAIDs such as diclofenac, does increase the risk of serious GI events [see Warnings and Precautions (5.2)].

Two large, controlled, clinical trials of a COX-2 selective NSAID for the treatment of pain in the first 10-14 days following CABG surgery found an increased incidence of myocardial infarction and stroke [see Contraindications (4)].

5.2 Gastrointestinal Effects – Risk of GI Ulceration, Bleeding, and Perforation

NSAIDs, including diclofenac, can cause serious gastrointestinal (GI) events including bleeding, ulceration, and perforation of the stomach, small intestine or large intestine, which can be fatal. These serious adverse events can occur at any time, with or without warning symptoms, in patients treated with NSAIDs. Only one in five patients who develop a serious upper GI adverse event on NSAID therapy is symptomatic. Upper GI ulcers, gross bleeding, or perforation caused by NSAIDs occur in approximately 1% of patients treated for 3-6 months, and in about 2-4% of patients treated for one year. These trends continue with longer duration of use, increasing the likelihood of developing a serious GI event at some time during the course of therapy. However, even short-term therapy is not without risk.

NSAIDs should be prescribed with extreme caution in patients with a prior history of ulcer disease or gastrointestinal bleeding. Patients with a prior history of peptic ulcer disease and/or gastrointestinal bleeding who use NSAIDs have a greater than 10-fold increased risk for developing a GI bleed compared to patients with neither of these risk factors. Other factors that increase the risk of GI bleeding in patients treated with NSAIDs include concomitant use of oral corticosteroids or anticoagulants, longer duration of NSAIDs therapy, smoking, use of alcohol, older age, and poor general health status. Most spontaneous reports of fatal GI events are in elderly or debilitated patients and therefore special care should be taken in treating this population.

To minimize the potential risk for an adverse GI event, the lowest effective dose should be used for the shortest possible duration. Physicians and patients should remain alert for signs and symptoms of GI ulceration and bleeding during diclofenac therapy and promptly initiate additional evaluation and treatment if a serious GI adverse event is suspected. For high-risk patients, alternate therapies that do not involve NSAIDs should be considered.

5.3 Hepatic Effects

Elevations of one or more liver tests may occur during therapy with diclofenac sodium. These laboratory abnormalities may progress, may remain unchanged, or may be transient with continued therapy. Borderline elevations (i.e. less than 3 times the ULN [ULN = the upper limit of normal range]) or greater elevations of transaminases occurred in about 15% of diclofenac-treated patients. Of the markers of hepatic function, ALT (SGPT) is recommended for the monitoring of liver injury.

In clinical trials, meaningful elevations (i.e., more than 3 times the ULN) of AST (GOT) (ALT was not measured in all studies) occurred in about 2% of approximately 5,700 patients at some time during diclofenac treatment. In a large, open-label, controlled trial of 3,700 patients treated for 2-6 months, patients were monitored first at 8 weeks and 1,200 patients were monitored again at 24 weeks. Meaningful elevations of ALT and/orAST occurred in about 4% of patients and included marked elevations (i.e., more than 8 times the ULN) in about 1% of the 3,700 patients. In that open-label study, a higher incidence of borderline (less than 3 times the ULN), moderate (3-8 times the ULN), and marked (>8 times the ULN) elevations of ALT or AST was observed in patients receiving diclofenac when compared to other NSAIDs. Elevations in transaminases were seen more frequently in patients with osteoarthritis than in those with rheumatoid arthritis.

Almost all meaningful elevations in transaminases were detected before patients became symptomatic. Abnormal tests occurred during the first 2 months of therapy with diclofenac in 42 of the 51 patients in all trials who developed marked transaminase elevations.

In postmarketing reports, cases of drug-induced hepatotoxicity have been reported in the first month, and in some cases, the first 2 months of therapy, but can occur at any time during treatment with diclofenac. Postmarketing surveillance has reported cases of severe hepatic reactions, including liver necrosis, jaundice, fulminant hepatitis with and without jaundice, and liver failure. Some of these reported cases resulted in fatalities or liver transplantation.

Physicians should measure transaminases periodically in patients receiving long-term therapy with diclofenac, because severe hepatotoxicity may develop without a prodrome of distinguishing symptoms. The optimum times for making the first and subsequent transaminase measurements are not known. Based on clinical trial data and postmarketing experiences, transaminases should be monitored within 4 to 8 weeks after initiating treatment with diclofenac. However, severe hepatic reactions can occur at any time during treatment with diclofenac.

If abnormal liver tests persist or worsen, if clinical signs and/or symptoms consistent with liver disease develop, or if systemic manifestations occur (e.g., eosinophilia, rash, abdominal pain, diarrhea, dark urine, etc.), diclofenac sodium should be discontinued immediately. To minimize the possibility that hepatic injury will become severe between transaminase measurements, physicians should inform patients of the warning signs and symptoms of hepatotoxicity (e.g., nausea, fatigue, lethargy, diarrhea, pruritus, jaundice, right upper quadrant tenderness, and “flu-like” symptoms), and the appropriate action patients should take if these signs and symptoms appear.

To minimize the potential risk for an adverse liver related event in patients treated with diclofenac sodium, the lowest effective dose should be used for the shortest duration possible. Caution should be exercised in prescribing diclofenac sodium with concomitant drugs that are know to be potentially hepatotoxic (e.g., antibiotics, anti-epileptics).

5.4 Hypertension

NSAIDs, including Voltaren® Gel, can lead to the onset of new hypertension or worsening of preexisting hypertension, either of which may contribute to the increased incidence of cardiovascular events. Patients taking thiazides or loop diuretics may have impaired response to these therapies when taking NSAIDs. NSAIDs, including Voltaren® Gel should be used with caution in patients with hypertension. Blood pressure should be monitored closely during the initiation of therapy with Voltaren® Gel and throughout the course of therapy.

5.5 Congestive Heart Failure and Edema

Fluid retention and edema have been observed in some patients treated with NSAIDs, including Voltaren® Gel. Voltaren® Gel should be used with caution in patients with fluid retention or heart failure.

5.6 Renal Effects

Long-term administration of NSAIDs has resulted in renal papillary necrosis and other renal injury. Renal toxicity has also been seen in patients in whom renal prostaglandins have a compensatory role in the maintenance of renal perfusion. In these patients, administration of an NSAID may cause a dose-dependent reduction in prostaglandin formation and, secondarily, in renal blood flow, which may precipitate overt renal decompensation. Patients at greatest risk of this reaction are those with impaired renal function, heart failure, liver dysfunction, those taking diuretics and ACE-inhibitors, and the elderly. Discontinuation of NSAID therapy is usually followed by recovery to the pretreatment state.

No information is available from controlled clinical studies regarding the use of Voltaren® Gel in patients with advanced renal disease. Therefore, treatment with Voltaren® Gel is not recommended in patients with advanced renal disease. If Voltaren® Gel therapy is initiated, close monitoring of the patient's renal function is advisable.

5.7 Anaphylactoid Reactions

As with other NSAIDs, anaphylactoid reactions may occur in patients without prior exposure to Voltaren® Gel. Voltaren® Gel should not be given to patients with the aspirin triad. This symptom complex typically occurs in asthmatic patients who experience rhinitis with or without nasal polyps, or who exhibit severe, potentially fatal bronchospasm after taking aspirin or other NSAIDs [see Contraindications (4), Warnings and Precautions (5.7)]. Emergency help should be sought in cases where an anaphylactoid reaction occurs.

5.8 Skin Reactions

NSAIDs, including Voltaren® Gel, can cause serious skin adverse events such as exfoliative dermatitis, Stevens-Johnson Syndrome (SJS), and toxic epidermal necrolysis (TEN), which can be fatal. These serious events may occur without warning. Patients should be informed about the signs and symptoms of serious skin manifestations, and the use of the drug should be discontinued at the first appearance of skin rash or any other signs of hypersensitivity.

Voltaren® Gel should not be applied to open skin wounds, infections, inflammations, or exfoliative dermatitis, as it may affect absorption and tolerability of the drug. Voltaren® Gel should not be allowed to come into contact with the eyes or with mucous membranes.

The effect of Voltaren® Gel under occlusive dressings has not been evaluated, and should be avoided.

5.9 Pregnancy

As with other NSAIDs, Voltaren® Gel should be avoided in late pregnancy, because it may cause premature closure of the ductus arteriosus.

5.10 Corticosteroid treatment

Voltaren® Gel cannot be expected to substitute for corticosteroids or to treat corticosteroid insufficiency. Abrupt discontinuation of corticosteroids may lead to exacerbation of corticosteroid-responsive illness. Patients on prolonged corticosteroid therapy should have their therapy tapered slowly if a decision is made to discontinue corticosteroids.

5.11 Inflammation

The pharmacological activity of diclofenac in reducing inflammation, and possibly fever, may diminish the utility of these diagnostic signs in detecting infectious complications of presumed noninfectious, painful conditions.

5.12 Hematological Effects

Anemia is sometimes seen in patients receiving NSAIDs. This may be due to fluid retention, occult or gross GI blood loss, or an incompletely described effect upon erythropoeisis. Patients on long-term treatment with NSAIDs, including Voltaren® Gel, should have their hemoglobin or hematocrit checked if they exhibit any signs or symptoms of anemia or blood loss.

NSAIDs inhibit platelet aggregation and have been shown to prolong bleeding time in some patients. Unlike aspirin, their effect on platelet function is quantitatively less, of shorter duration, and reversible. Patients treated with Voltaren® Gel who may be adversely affected by alteration in platelet function, such as those with coagulation disorders or patients receiving anticoagulants should be carefully monitored.

5.13 Preexisting Asthma

Patients with asthma may have aspirin-sensitive asthma. The use of aspirin in patients with aspirin sensitive asthma has been associated with severe bronchospasm, which can be fatal. Since cross reactivity, including bronchospasm, between aspirin and other nonsteroidal anti-inflammatory drugs has been reported in such aspirin-sensitive patients, Voltaren® Gel should not be administered to patients with this form of aspirin sensitivity and should be used with caution in patients with preexisting asthma.

5.14 Sun Exposure

Patients should minimize or avoid exposure to natural or artificial sunlight on treated areas because studies in animals indicated topical diclofenac treatment resulted in an earlier onset of ultraviolet light induced skin tumors. The potential effects of Voltaren® Gel on skin response to ultraviolet damage in humans are not known.

5.15 Eye Exposure

Contact of Voltaren® Gel with eyes and mucosa, although not studied, should be avoided. Patients should be advised that if eye contact occurs, they should immediately wash out the eye with water or saline and consult a physician if irritation persists for more than an hour.

5.16 Laboratory Tests

Because serious GI tract ulcerations and bleeding can occur without warning symptoms, physicians should monitor for signs or symptoms of GI bleeding. Patients on long-term treatment with NSAIDs, should have a CBC and a chemistry profile checked periodically. If abnormal liver tests or renal tests persist or worsen, Voltaren® Gel should be discontinued.

ADVERSE REACTIONS SECTION

6.1 Clinical Studies Experience

Because clinical trials are conducted under widely varying conditions, adverse reaction rates observed in the clinical trials of a drug cannot be directly compared with rates in the clinical trials of another drug and may not reflect the rates observed in practice.

During clinical development, 913 patients were exposed to Voltaren® Gel in randomized, double-blind, multicenter, vehicle-controlled, parallel-group studies in osteoarthritis of the superficial joints of the extremities. Of these, 513 patients received Voltaren® Gel for osteoarthritis of the knee and 400 were treated for osteoarthritis of the hand. Additionally, 583 patients were exposed to Voltaren® Gel in an uncontrolled, open-label, long-term safety trial in osteoarthritis of the knee. Of these, 355 patients were treated for osteoarthritis of 1 knee and 228 were treated for osteoarthritis of both knees. Duration of exposure ranged from 8 to 12 weeks for the placebo-controlled studies, and up to 12 months for the open-label safety trial.

Short-Term Placebo-Controlled Trials:

Adverse reactions observed in at least 1% of patients treated with Voltaren® Gel:

Non-serious adverse reactions that were reported during the short-term placebo-controlled studies comparing Voltaren® Gel and placebo (vehicle gel) over study periods of 8 to 12 weeks (16 g per day), were application site reactions. These were the only adverse reactions that occurred in > 1% of treated patients with a greater frequency in the Voltaren® Gel group (7%) than the placebo group (2%).

Table 1 lists the types of application site reactions reported. Application site dermatitis was the most frequent type of application site reaction and was reported by 4% of patients treated with Voltaren® Gel, compared to 1% of placebo patients.

Table 1: Non-serious Application Site Adverse Reactions (≥ 1% Voltaren® Gel Patients) – Short-term Controlled Trials
Adverse Reaction† | Voltaren® Gel N = 913 | Placebo (vehicle) N = 876
 | N (%) | N (%)
Any application site reaction | 62 (7) | 19 (2)
Application site dermatitis | 32 (4) | 6 (<1)
Application site pruritus | 7 (<1) | 1 (<1)
Application site erythema | 6 (<1) | 3 (<1)
Application site paresthesia | 5 (<1) | 3 (<1)
Application site dryness | 4 (<1) | 3 (<1)
Application site vesicles | 3 (<1) | 0
Application site irritation | 2 (<1) | 0
Application site papules | 1 (<1) | 0

†Preferred Term according to MedDRA 9.1.

In the placebo-controlled trials, the discontinuation rate due to adverse reactions was 5% for patients treated with Voltaren® Gel, and 3% for patients in the placebo group. Application site reactions, including application site dermatitis, were the most frequent reason for treatment discontinuation.

Long-term Open-label Safety Trial:

In the open-label, long-term safety study, distribution of adverse reactions was similar to that in the placebo-controlled studies. In this study, where patients were treated for up to 1 year with Voltaren® Gel up to 32 g per day, application site dermatitis was observed in 11% of patients. Adverse reactions that led to the discontinuation of the study drug were experienced in 12% of patients. The most common adverse reaction that led to discontinuation of the study was application site dermatitis, which was experienced by 6% of patients.

DRUG INTERACTIONS SECTION

7.1 Aspirin

When diclofenac is administered with aspirin, the binding of diclofenac to protein is reduced, although the clearance of free diclofenac is not altered. The clinical significance of this interaction is not known; however, as with other NSAIDs, concomitant administration of diclofenac and aspirin is not generally recommended because of the potential of increased adverse effects.

7.2 Anticoagulants

The effects of anticoagulants such as warfarin and NSAIDs on GI bleeding are synergistic, such that users of both drugs together have a risk of serious GI bleeding higher than users of either drug alone.

7.3 ACE-Inhibitors

NSAIDs may diminish the antihypertensive effect of angiotensin converting enzyme (ACE) inhibitors. This interaction should be given consideration in patients taking NSAIDs concomitantly with ACE-inhibitors.

7.4 Diuretics

Clinical studies, as well as post-marketing observations, have shown that NSAIDs can reduce the natriuretic effect of furosemide and thiazides in some patients. The response has been attributed to inhibition of renal prostaglandin synthesis. During concomitant therapy with NSAIDs, the patient should be observed closely for signs of renal failure [see Warnings and Precautions (5.6)], as well as to assure diuretic efficacy.

7.5 Lithium

NSAIDs have produced an elevation of plasma lithium levels and a reduction in renal lithium clearance. The mean minimum lithium concentration increased 15% and the renal clearance was decreased by approximately 20%. These effects have been attributed to inhibition of renal prostaglandin synthesis by the NSAID. Thus, when NSAIDs, including diclofenac, and lithium are administered concurrently, patients should be observed carefully for signs of lithium toxicity.

7.6 Methotrexate

NSAIDs have been reported to competitively inhibit methotrexate accumulation in rabbit kidney slices. This may indicate that they could enhance the toxicity of methotrexate. Caution should be used when NSAIDs, including diclofenac, are administered concomitantly with methotrexate.

7.7 Cyclosporine

Diclofenac, like other NSAIDs, may affect renal prostaglandins and increase the toxicity of certain drugs. Therefore concomitant therapy with diclofenac may increase cyclosporine’s nephrotoxicity. Caution should be used when diclofenac is administered concomitantly with cyclosporine.

7.8 Oral Nonsteroidal Anti-inflammatory Drugs

Specific interaction studies of Voltaren® Gel and oral NSAIDs were not performed. Also, the clinical trials of Voltaren® Gel prohibited concomitant use of oral NSAIDS. There is systemic exposure to diclofenac following normal use of Voltaren® Gel, up to 6% of the systemic levels of a single oral dose of diclofenac sodium. [see Clinical Pharmacology (12.3)] Therefore, concomitant administration of Voltaren® Gel with oral NSAIDs or aspirin may result in increased adverse NSAID effects.

7.9 Topical Treatments

Concomitant use of Voltaren® Gel with other topical products, including topical medications, sunscreens, lotions, moisturizers, and cosmetics, on the same skin site has not been tested and should be avoided because of the potential to alter local tolerability and absorption.

USE IN SPECIFIC POPULATIONS SECTION

8.1 Pregnancy

The safety of Voltaren® Gel has not been established during pregnancy. There are no well-controlled studies of diclofenac in pregnant women. Human and animal studies indicate that diclofenac crosses the placenta. In late pregnancy, as with other NSAIDs, Voltaren® Gel should be avoided because it may cause premature closure of the ductus arteriosus.

Teratogenic effects

Pregnancy Category C: Studies in mice, rats, and rabbits in which diclofenac was administered orally throughout gestation revealed no evidence of teratogenicity despite the induction of maternal toxicity and fetal toxicity corresponding to a human equivalent dose approximately 4.5-, 2-, and 9-fold (mouse, rat, rabbit, respectively) of the maximum human topical dose of Voltaren® Gel (based on bioavailability and body surface area comparison).

Nonteratogenic effects

The use of diclofenac, as with other NSAIDs, is associated with the adverse fetal cardiovascular effect of premature closure of the ductus arteriosus.

8.2 Labor and Delivery

In rat studies with oral NSAIDs, including diclofenac, as with other drugs known to inhibit prostaglandin synthesis, there is an increased incidence of dystocia and delayed parturition corresponding to a human equivalent dose approximately similar to the maximum recommended clinical dose (based on bioavailability and body surface area comparison). The effects of Voltaren® Gel on labor and delivery in pregnant women are unknown.

8.3 Nursing Mothers

It is not known whether diclofenac is excreted in human milk; however, studies in animals detected diclofenac in the milk after oral administration. Because many drugs are excreted in human milk and because of the potential for serious adverse reactions in nursing infants from Voltaren® Gel a decision should be made whether to discontinue nursing or to discontinue the drug, taking into account the importance of the drug to the mother.

8.4 Pediatric Use

Safety and effectiveness in pediatric patients have not been established.

8.5 Geriatric Use

Of the total number of subjects treated with Voltaren® Gel in clinical studies, 498 were 65 years of age and over. No overall differences in effectiveness or safety were observed between these subjects and younger subjects, but greater sensitivity to the effect of NSAIDs in some older individuals cannot be ruled out.

Diclofenac, as with any NSAID, is known to be substantially excreted by the kidney, and the risk of toxic reactions to Voltaren® Gel may be greater in patients with impaired renal function. Because elderly patients are more likely to have decreased renal function, care should be taken when using Voltaren® Gel in the elderly, and it may be useful to monitor renal function.

OVERDOSAGE SECTION

There has been no experience of overdose with Voltaren® Gel.

No events of accidental ingestion have been reported with Voltaren® Gel. Effects similar to those observed after an overdose of diclofenac tablets can be expected if substantial amounts of Voltaren® Gel are ingested. Symptoms following acute oral NSAID overdoses are usually limited to lethargy, drowsiness, nausea, vomiting, and epigastric pain, which are generally reversible with supportive care. Gastrointestinal bleeding can occur. Hypertension, acute renal failure, respiratory depression, and coma may occur. Anaphylactoid reactions have been reported with therapeutic ingestion of NSAIDs, and may occur after an overdose.

In the event of oral ingestion resulting in significant systemic side effects, it is recommended that the stomach be emptied by vomiting or lavage. Forced diuresis may theoretically be beneficial because the drug is excreted in the urine. The effect of dialysis or hemoperfusion in the elimination of diclofenac (99% protein-bound) remains unproven. In addition to supportive measures, the use of oral activated charcoal may help to reduce the absorption of diclofenac. Supportive and symptomatic treatment should be given for complications such as renal failure, convulsions, gastrointestinal irritation, and respiratory depression.

For additional information about overdose treatment, call a poison control center (1-800-222-1222).

DESCRIPTION SECTION

Voltaren® Gel (diclofenac sodium topical gel) is a nonsteroidal anti-inflammatory drug (NSAID) for topical use only. It contains the active ingredient, diclofenac sodium, in an opaque, white gel base. Diclofenac sodium is a white to slightly yellow crystalline powder. Diclofenac sodium is a benzene–acetic acid derivative. The chemical name is 2-[(2,6-dichlorophenyl)amino]benzeneacetic acid, monosodium salt. The molecular weight is 318.14. Its molecular formula is C14H10C12NNaO2. It has the following structural formula:

Voltaren® Gel also contains carbomer homopolymer Type C, cocoyl caprylocaprate, fragrance, isopropyl alcohol, mineral oil, polyoxyl 20 cetostearyl ether, propylene glycol, purified water, and strong ammonia solution.

CLINICAL PHARMACOLOGY SECTION

12.1 Mechanism of Action

The mechanism of action of diclofenac is similar to that of other nonsteroidal anti-inflammatory drugs. Diclofenac inhibits the enzyme, cyclooxygenase (COX), an early component of the arachidonic acid cascade, resulting in the reduced formation of prostaglandins, thromboxanes and prostacylin. It is not completely understood how reduced synthesis of these compounds results in therapeutic efficacy.

12.2 Pharmacodynamics

Diclofenac, the active component of Voltaren® Gel has anti-inflammatory, anti-nociception, and antipyretic effects.

12.3 Pharmacokinetics

The pharmacokinetics of Voltaren® Gel were assessed in healthy volunteers following repeated applications during 7 days of Voltaren® Gel to 1 knee (4 x 4 g per day) or to 2 knees and 2 hands (4 x 12 g per day) versus the recommended oral dose of diclofenac sodium for the treatment of osteoarthritis (3 x 50 mg per day). A summary of the pharmacokinetic parameters is presented in Table 2.

Table 2. Pharmacokinetic Parameters and Comparison of Voltaren® Gel to Oral Diclofenac Sodium Tablets After Repeated Administration
Treatment | Cmax (ng/mL) Mean ± SD % of Oral (CI) | tmax (hr) Median (range) | AUC0-24 (ng•h/mL) Mean ± SD % of Oral (CI)
Voltaren® Gel 4 x 4 g per day (=160 mg diclofenac sodium per day) | 15± 7.3 0.6% (0.5-0.7) | 14 (0-24) | 233 ± 128 5.8% (5-6.7)
Voltaren® Gel 4 x 12 g per day (=480 mg diclofenac sodium per day) | 53.8 ± 32 2.2% (1.9-2.6) | 10 (0-24) | 807 ± 478 19.7% (17-22.8)
Diclofenac sodium tablets, orally 3 x 50 mg per day (=150 mg diclofenac sodium per day) | 2270 ± 778 100% | 6.5 (1-14) | 3890 ± 1710 100%

Cmax = maximum plasma concentration; tmax = time of Cmax; AUC0-24 = area

under the concentration-time curve; SD = standard deviation; CI = confidence interval.

Systemic exposure (area under the concentration-time curve) and maximum plasma concentrations of diclofenac are significantly lower with Voltaren® Gel than with comparable oral treatment of diclofenac sodium.

Systemic exposure with recommended use of Voltaren® Gel (4 x 4 g per day applied to 1 knee) is on average 17 times lower than with oral treatment. (Basis: treatment with Voltaren® Gel of 1 knee, 4 times a day versus 50 mg, 3 times a day of oral diclofenac tablets). The amount of diclofenac sodium that is systemically absorbed from Voltaren® Gel is on average 6% of the systemic exposure from an oral form of diclofenac sodium.

The average peak plasma concentration with recommended use of Voltaren® Gel (4 x 4 g per day applied to 1 knee) is 158 times lower than with the oral treatment.

The pharmacokinetics of Voltaren® Gel has been tested under conditions of moderate heat (application of a heat patch for 15 minutes prior to gel application) and of moderate exercise (first gel application followed by a 20-minute treadmill exercise). No clinically relevant differences of systemic absorption and of tolerability were found between applications of Voltaren® Gel (4 x 4 g per day on 1 knee) with and under the conditions tested. However, the pharmacokinetics of Voltaren® Gel were not tested under the condition of heat application following gel application. Therefore, concurrent use of Voltaren® Gel and heat is not recommended.

NONCLINICAL TOXICOLOGY SECTION

13.1 Carcinogenesis, Mutagenesis, Impairment of Fertility

Carcinogenicity studies in mice and rats administered diclofenac sodium as a dietary constituent for 2 years at does up to 2 mg/kg/day resulted in no significant increases in tumor incidence corresponding to a human equivalent dose approximately 0.5- and 1-fold (mouse and rat, respectively) of the maximum human topical dose of Voltaren® Gel (based on bioavailability and body surface area comparison).

In a dermal carcinogenicity study conducted in albino mice, daily topical applications of a diclofenac sodium gel product for two years at concentrations up to 0.035% diclofenac sodium (a 29-fold lower diclofenac sodium concentration than present in Voltaren® Gel) did not increase neoplasm incidence.

In a photococarcinogenicity study conducted in hairless mice, topical application of a diclofenac sodium gel product at doses up to 0.035% diclofenac sodium (a 29-fold lower diclofenac sodium concentration than present in Voltaren® Gel) resulted in an earlier median time of onset of tumors.

Diclofenac was not mutagenic or clastogenic in a battery of genotoxicity tests that included the bacterial reverse mutation assay, in vitro mouse lymphoma point mutation assay, chromosomal aberration studies in Chinese hamster ovarian cells in vitro, and in vivo rat chromosomal aberration assay of bone marrow cells.

Diclofenac did not affect male or female fertility in rats at doses up to 4 mg/kg/day which induced toxicity, corresponding to a human equivalent dose approximately 2-fold greater than the maximum human topical dose of Voltaren® Gel (based on bioavailability and body surface area comparison).

CLINICAL STUDIES SECTION

14.1 Pivotal Studies in Osteoarthritis of the Superficial Joints of the Extremities

Study 1 evaluated the efficacy of Voltaren® Gel for the treatment of osteoarthritis of the knee in a 12-week, randomized, double-blind, multicenter, placebo-controlled, parallel-group trial. Voltaren® Gel was administered at a dose of 4 g, 4 times daily, on 1 knee (16 g per day). Pain as assessed by the patients at Week 12 using the WOMAC (Western Ontario and McMaster Universities Osteoarthritis Index) Pain Subindex was lower in the Voltaren® Gel group than the placebo group.

Study 2 evaluated the efficacy of Voltaren® Gel for the treatment of osteoarthritis in subjects with osteoarthritis of the hand in an 8-week, randomized, double-blind, multicenter, placebo-controlled, parallel-group study. Voltaren® Gel was administered at a dose of 2 g per hand, 4 times daily, on both hands (16 g per day). Pain in the target hand as assessed by the patients at Weeks 4 and 6 on a visual analog scale from 0 to 100 was lower in the Voltaren® Gel group than the placebo group.

Table 3. Efficacy outcomes of Voltaren® Gel in Studies 1 and 2
 |  | Voltaren® Gel | Placebo (Vehicle) | Adjusted Difference (Placebo - Voltaren® Gel)
Study 1 (Knee) WOMAC Pain * # at Week 12 | Sample Size | 127 | 119
 | Mean outcome | 28 | 37 | ∆ = 7†
 | 95% confidence interval |  |  | (1, 12)
Study 2 (Hand) Pain Intensity # at Week 4 | Sample size | 198 | 187
 | Mean outcome | 43 | 50 | ∆ = 7 ††
 | 95% confidence interval |  |  | (2, 12)
Study 2 (Hand) Pain Intensity # at Week 6 | Sample size | 198 | 187
 | Mean outcome | 40 | 47 | ∆ = 7 ††
 | 95% confidence interval |  |  | (1, 13)

* WOMAC = Western Ontario McMaster Osteoarthritis Index.

# Scale from 0 (best) to 100 (worst),

† Difference is adjusted using an analysis of covariance (ANCOVA) model with main effects of treatment and center and baseline covariate.

†† Difference is adjusted using an analysis of covariance (ANCOVA) model with main effects of treatment, center, indicator for pain in the CMC-1 joint, and baseline as a covariate, and the treatment-by-CMC-1 indicator interaction. Difference is weighted by size of CMC-1 strata

HOW SUPPLIED SECTION

Voltaren® Gel is available in tubes containing 100 g of the topical gel in each tube. Physician samples are packaged in 20 g tubes. Each tube contains diclofenac sodium in a gel base (10 mg of diclofenac sodium per gram of gel or 1%).

20 gram tube (physician’s sample) NDC 63481-684-83

100 gram tube NDC 63481-684-47

3 Carton (3 Tubes containing 100 gram each) NDC 63481-684-03

5 Carton (5 Tubes containing 100 gram each) NDC 63481-684-05

Storage

Store at 25°C (77°F); excursions permitted to 15-30°C (59-86°F) [See USP Controlled Room Temperature]

Keep from freezing.

PATIENT MEDICATION INFORMATION SECTION

Also See Section 18 Medical Guide Below.

17.1 Medication Guide

Patients should be informed of the following information before initiating therapy with an NSAID and periodically during the course of ongoing therapy. Patients should be informed of the availability of a Medication Guide for Non-Steroidal Anti-inflammatory Drugs (NSAIDs), and they should be instructed to read the Medication Guide prior to using Voltaren® Gel.

17.2 Cardiovascular effects

Voltaren® Gel, like other NSAIDs, may cause serious CV side effects, such as MI or stroke, which may result in hospitalization and even death. Although serious CV events can occur without warning symptoms, patients should be alert for the signs and symptoms of chest pain, shortness of breath, weakness, slurring of speech, and should ask for medical advice when observing any indicative sign or symptoms. Patients should be apprised of the importance of this follow-up [see Warnings and Precautions (5.1)].

17.3 Gastrointestinal effects

Voltaren® Gel, like other NSAIDs, can cause GI discomfort and, rarely, more serious GI side effects, such as ulcers and bleeding, which may result in hospitalization and even death. Although serious GI tract ulcerations and bleeding can occur without warning symptoms, patients should be alert for the signs and symptoms of ulcerations and bleeding, and should ask for medical advice when observing any indicative sign or symptoms including epigastric pain, dyspepsia, melena, and hematemesis. Patients should be apprised of the importance of this follow-up [see Warnings and Precautions (5.2)].

17.4 Hepatotoxicity

Patients should be informed of the warning signs and symptoms of hepatotoxicity (e.g., nausea, fatigue, lethargy, diarrhea, pruritus, jaundice, right upper quadrant tenderness, and “flu-like” symptoms). If these occur, patients should be instructed to stop therapy with Voltaren® Gel and seek immediate medical therapy [see Warnings and Precautions (5.3)].

17.5 Adverse Skin Reactions

Voltaren® Gel, like other NSAIDs, can cause serious skin side effects such as exfoliative dermatitis, SJS, and TEN, which may result in hospitalizations and even death. Although serious skin reactions may occur without warning, patients should be alert for the signs and symptoms of skin rash and blisters, fever, or other signs of hypersensitivity such as itching, and should ask for medical advice when observing any indicative signs or symptoms [see Warnings and Precautions (5.8)].

Patients should be advised to stop Voltaren® Gel immediately if they develop any type of rash and contact their physicians as soon as possible.

Patients should be instructed not to apply Voltaren® Gel to open skin wounds, infections, inflammations, or exfoliative dermatitis, as it may affect absorption and tolerability of the drug.

Patients should be instructed to avoid concomitant use of Voltaren® Gel with other topical products, including sunscreens, cosmetics lotions, moisturizers, insect repellants, on the treated skin site. Concomitant use may result in skin reactions or change the absorption of Voltaren® Gel.

Patients should be instructed to minimize or avoid exposure of treated areas to natural or artificial sunlight.

17.6 Weight gain and edema

Patients should promptly report to their physicians signs or symptoms of unexplained weight gain or edema following treatment with Voltaren® Gel [see Warnings and Precautions (5.5)].

17.7 Anaphylactoid reactions

Patients should be informed of the signs of an anaphylactoid reaction (e.g., difficulty breathing, swelling of the face or throat). If these occur, patients should be instructed to seek immediate emergency help [see Warnings and Precautions (5.7)].

17.8 Effects during pregnancy

In late pregnancy, as with other NSAIDs, Voltaren® Gel should be avoided because it will cause premature closure of the ductus arteriosus [see Warnings and Precautions (5.9)].

17.9 Eye Exposure

Patients should be instructed to avoid contact of Voltaren® Gel with the eyes and mucosa, although not studied, should be avoided. Patients should be advised that if eye contact occurs, they should immediately wash out the eye with water or saline and consult a physician if irritation persists for more than an hour.

Comments or Questions?

Call toll-free 1-800-452-0051

Marketed by:
Endo Pharmaceuticals Inc.
Chadds Ford, PA 19317

Manufactured for:
Novartis Consumer Health, Inc.
Parsippany, NJ 07054

Manufactured by:
Novartis Pharma Produktions GmbH
Wehr, Germany

©2009 Novartis Consumer Health, Inc., Parsippany, NJ 07054. All Trademarks owned and licensed by Novartis AG

42035D / October 2009

SPL MEDGUIDE SECTION

Medication GuideforNon-steroidal Anti-Inflammatory Drugs (NSAIDs)

(See the end of this Medication Guide for a list of prescription NSAID medicines.)

What is the most important information I should know about medicines called Non-Steroidal Anti-Inflammatory Drugs (NSAIDs)?

NSAID medicines may increase the chance of a heart attack or stroke that can lead to death. This chance increases:

- with longer use of NSAID medicines
- in people who have heart disease

NSAID medicines should never be used right before or after a heart surgery called a “coronary artery bypass graft (CABG).”

NSAID medicines can cause ulcers and bleeding in the stomach and intestines at any time during treatment. Ulcers and bleeding:

- can happen without warning symptoms
- may cause death

The chance of a person getting an ulcer or bleeding increases with:

- taking medicines called “corticosteroids” and “anticoagulants”
- longer use
- smoking
- drinking alcohol
- older age
- having poor health

NSAID medicines should only be used:

- exactly as prescribed
- at the lowest dose possible for your treatment
- for the shortest time needed

What are Non-Steroidal Anti-Inflammatory Drugs (NSAIDs)?

NSAID medicines are used to treat pain and redness, swelling, and heat (inflammation) from medical conditions such as:

- different types of arthritis
- menstrual cramps and other types of short-term pain

Who should not take a Non-Steroidal Anti-Inflammatory Drug (NSAID)?

Do not take an NSAID medicine:

- if you had an asthma attack, hives, or other allergic reaction with aspirin or any other NSAID medicine
- for pain right before or after heart bypass surgery

Tell your healthcare provider:

- about all of your medical conditions.
- about all of the medicines you take. NSAIDs and some other medicines can interact with each other and cause serious side effects. Keep a list of your medicines to show to your healthcare provider and pharmacist.

- if you are pregnant. NSAID medicines should not be used by pregnant women late in their pregnancy.
- if you are breastfeeding. Talk to your doctor.

What are the possible side effects of Non-Steroidal Anti-Inflammatory Drugs (NSAIDs)?

Serious side effects include:

- heart attack
- stroke
- high blood pressure
- heart failure from body swelling (fluid retention)
- kidney problems including kidney failure
- bleeding and ulcers in the stomach and intestine
- low red blood cells (anemia)
- life-threatening skin reactions
- life-threatening allergic reactions
- liver problems including liver failure
- asthma attacks in people who have asthma

Other side effects include:

- stomach pain
- constipation
- diarrhea
- gas
- heartburn
- nausea
- vomiting
- dizziness

Get emergency help right away if you have any of the following symptoms:

- shortness of breath or trouble breathing
- chest pain
- weakness in one part or side of your body

- slurred speech
- swelling of the face or throat

Stop your NSAID medicine and call your healthcare provider right away if you have any of the following symptoms:

- nausea
- more tired or weaker than usual
- itching
- your skin or eyes look yellow
- stomach pain
- flu-like symptoms
- vomit blood

- there is blood in your bowel movement or it is black and sticky like tar
- unusual weight gain
- skin rash or blisters with fever
- swelling of the arms and legs, hands and feet

These are not all the side effects with NSAID medicines. Talk to your healthcare provider or pharmacist for more information about NSAID medicines.

Other information about Non-Steroidal Anti-Inflammatory Drugs (NSAIDs):

- Aspirin is an NSAID medicine but it does not increase the chance of a heart attack. Aspirin can cause bleeding in the brain, stomach, and intestines. Aspirin can also cause ulcers in the stomach and intestines.
- Some of these NSAID medicines are sold in lower doses without a prescription (over-the-counter). Talk to your healthcare provider before using over-the-counter NSAIDs for more than 10 days.

NSAID medicines that need a prescription

Generic Name | Tradename
Celecoxib | Celebrex®
Diclofenac | Cataflam®, Voltaren®, Arthrotec™ (combined with misoprostol)
Diflunisal | Dolobid®
Etodolac | Lodine®, Lodine®XL
Fenoprofen | Nalfon®, Nalfon®200
Flurbirofen | Ansaid®
Ibuprofen | Motrin®, Tab-Profen®, Vicoprofen®* (combined with hydrocodone), Combunox™ (combined with oxycodone)
Indomethacin | Indocin®, Indocin®SR, Indo-Lemmon™, Indomethagan™
Ketoprofen | Oruvail®
Ketorolac | Toradol®
Mefenamic Acid | Ponstel®
Meloxicam | Mobic®
Nabumetone | Relafen®
Naproxen | Naprosyn®, Anaprox®, Anaprox®DS, EC-Naprosyn®, Naprelan®, Naprapac® (copackaged with lansoprazole)
Oxaprozin | Daypro®
Piroxicam | Feldene®
Sulindac | Clinoril®
Tolmetin | Tolectin®, Tolectin DS®, Tolectin®600

*Vicoprofen contains the same dose of ibuprofen as over-the-counter (OTC) NSAID, and is usually used for less than 10 days to treat pain. The OTC NSAID label warns that long term continuous use may increase the risk of heart attack or stroke.

This Medication Guide has been approved by the U.S. Food and Drug Administration.

Revised: June 2008

19 Patient Package Insert

Patient Instructions for Use

Your doctor has prescribed Voltaren® Gel to help relieve arthritis pain in some of your joints. Voltaren® Gel may be used to treat arthritis pain:

- In the arms: hands, wrists and elbows.
- In the legs: feet, ankles and knees.
- Use Voltaren® Gel exactly how your doctor prescribes it for you. Do not apply Voltaren® Gel anywhere other than where your doctor tells you to.
- Do not use more than a total of 32 grams of Voltaren® Gel each day. This means that if you add up the amount of Voltaren® Gel as directed by your doctor, it should not be more than 32 grams in one day.

The dose for your hands, elbows or wrists is 2 grams of Voltaren® Gel each time you apply it.

- Apply Voltaren® Gel 4 times a day (a total of 8 grams each day).
- Do not apply more than 8 grams each day to any one of your affected hands, wrists or elbows

The dose for your knees, ankles or feet is 4 grams of Voltaren® Gel each time you apply it.

- Apply Voltaren® Gel 4 times a day (a total of 16 grams each day)
- Do not apply more than 16 grams each day to any one of your affected knees, ankles or feet.

Some examples include:

- If you use 2 grams of Voltaren® Gel on one hand, 4 times a day, your total dose for one day is 8 grams
- If you use 4 grams of Voltaren® Gel on one knee, 4 times a day, your total dose for one day is 16 grams.
- Your total dose for one day, treating one hand and one knee, is 8 grams plus 16 grams, which equals 24 grams of Voltaren® Gel.
- Before you use a new tube of Voltaren® Gel for the first time, open the foil seal that covers the tube opening by using the spiked top of the cap. Remember to remove the dosing card from the carton.
- Apply Voltaren® Gel to clean, dry skin that does not have any cuts, infections or rashes.
- Do not use heating pads or apply bandages where you have applied Voltaren® Gel.
- Avoid exposing skin where you apply Voltaren® Gel to sunlight and artificial light, such as tanning booths.
- Do not use sunscreens, cosmetics, lotions, moisturizers, insect repellants, or other topical medicines on the same skin areas where you have applied Voltaren® Gel.
- Do not get Voltaren® Gel in your eyes, nose or mouth. Voltaren® Gel is only to be used on your skin (topical use). If you get Voltaren® Gel in your eyes, rinse your eyes right away with water or saline. Talk with your doctor if eye irritation lasts for more than one hour.

What to do if you miss a dose:

- If you miss a dose of Voltaren® Gel, continue with your next scheduled dose using the proper amount of Voltaren® Gel.
- Do not double the dose.

Applying Voltaren® Gel to hands, elbows or wrists:

1. The dose for each hand, elbow or wrist is 2 grams of Voltaren® Gel.

- Apply Voltaren® Gel 4 times a day (a total of 8 grams each day).
- Do not apply more than 8 grams each day to any one of your affected hands, wrists or elbows.

2. To measure the right amount of Voltaren® Gel, remove one dosing card from the package and place the card on a flat surface so that you can read the print. If the print is backwards, flip dosing card over. See the picture below.

3. Squeeze Voltaren® Gel onto the dosing card evenly, up to the 2 gram line. Make sure the gel covers the entire 2 gram area of the dosing card as shown in the picture below. Put the cap back on the tube of Voltaren® Gel.

4. Apply the gel to your elbow, wrist, or hand. You can use the dosing card to apply the gel.. The hands should be used to gently rub the gel into the skin. Do not share the dosing card with another person.

Make sure to cover the entire affected elbow, wrist or hand with the gel. Remember that the hand includes the palm of your hand, the top of your hand and your fingers.

5. After using the dosing card, hold end with fingertips, rinse and dry. Store dosing card until next use. Store out of reach of children.

6. Do not shower or bathe for at least 1 hour after applying Voltaren® Gel. Do not wash your treated hand for at least 1 hour after

applying Voltaren® Gel.

7. Wait 10 minutes before covering the treated skin with gloves or clothing..

Applying Voltaren® Gel to knees, ankles, or feet:

1. The dose for each knee, ankle or foot is 4 grams of Voltaren® Gel.

- Apply Voltaren® Gel 4 times a day (a total 16 grams each day).
- Do not apply more than 16 grams each day to any one of your affected knees, ankles or feet.

2. To measure the right amount of Voltaren® Gel, place the dosing card on a flat surface so that you can read the print. If the print is

backwards, flip dosing card over. See the picture below.

3. Squeeze Voltaren® Gel onto the dosing card evenly up to the 4 gram line, making sure the gel covers the entire 4 gram area of the dosing card, as shown in the picture below. Put the cap back on the tube of Voltaren® Gel.

4. Apply Voltaren® Gel to foot, ankle or knee and gently rub the gel into the skin.

- You can use the dosing card to apply the gel.
- Make sure to cover the entire foot, ankle or knee area with the gel.

For example, cover the skin above, below, inside and outside the knee cap. Remember that the foot includes the sole of your foot, the top of your foot and your toes.

5. After using the dosing card, fold the used dosing card in half (application side inside) and throw it away in a safe place out of the reach of children and pets.

6. Do not shower or bathe for 1 hour after application.
7. Wait 10 minutes before covering the treated skin with clothing.

8. Wash your hands after applying Voltaren® Gel to your foot, ankle or knee.

Store Voltaren® Gel at room temperature, 59° F to 86°F (15°C to 30°C).

All registered trademarks in this document are the property of their respective owners.

Comments or Questions?

Call toll-free 1-800-452-0051

Marketed by:
Endo Pharmaceuticals Inc.
Chadds Ford, PA 19317

Manufactured for:
Novartis Consumer Health, Inc.
Parsippany, NJ 07054

Manufactured by:
Novartis Pharma Produktions GmbH
Wehr, Germany

©2009 Novartis Consumer Health, Inc., Parsippany, NJ 07054. All Trademarks owned and licensed by Novartis AG

42035D/ October 2009